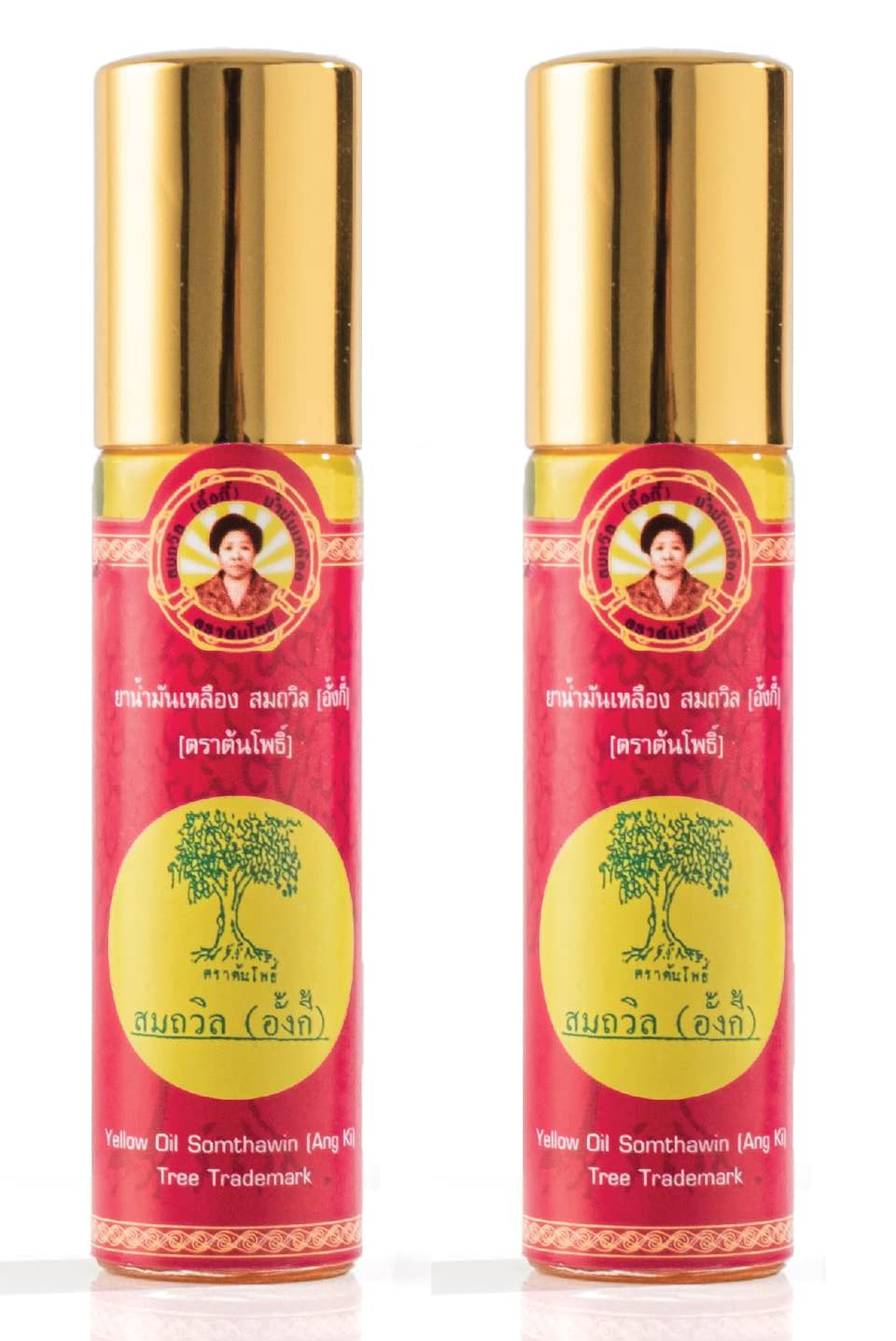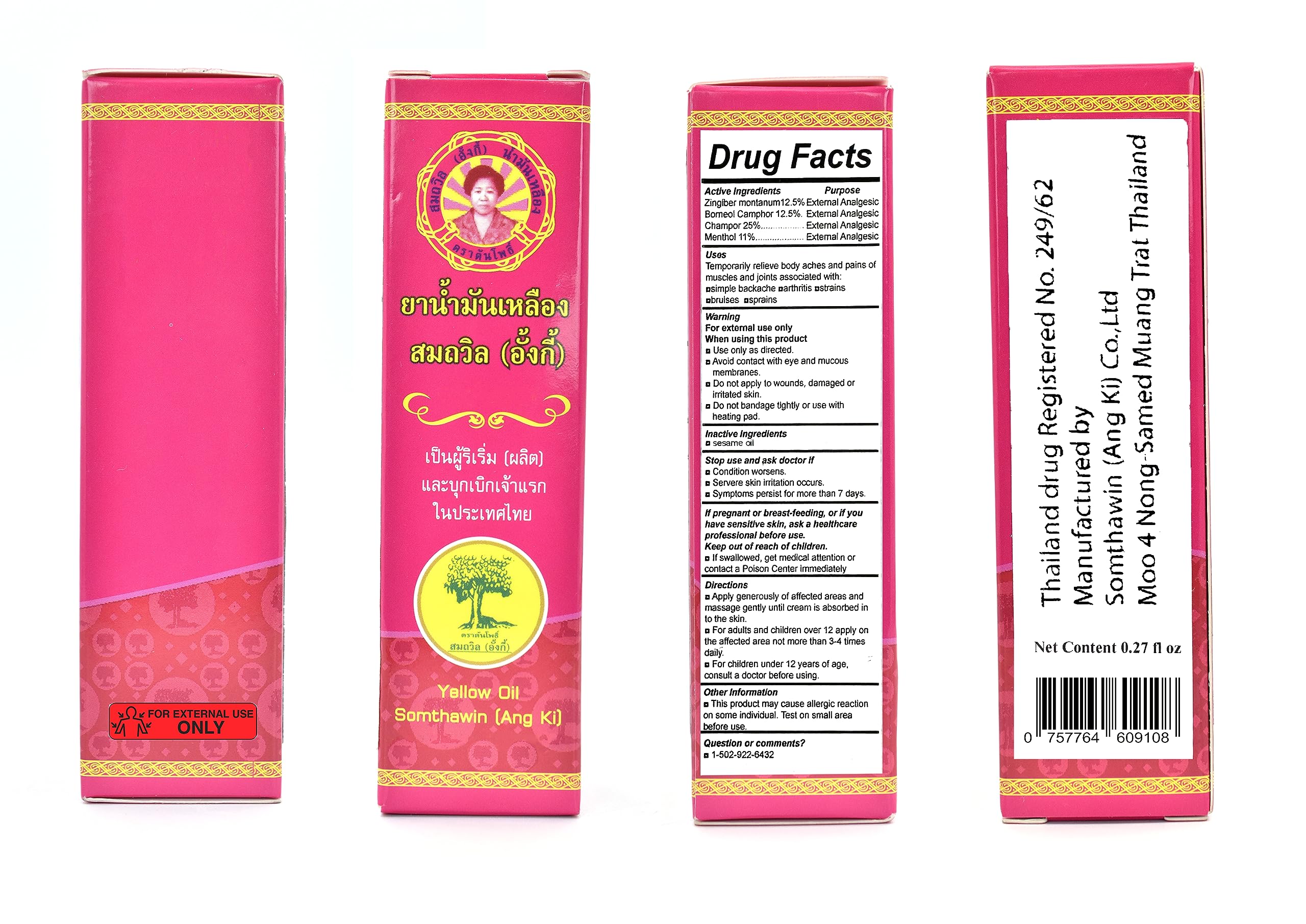 DRUG LABEL: Somthawin Angki Thai Aroma Herb Yellow Oil
NDC: 84212-334 | Form: SOLUTION
Manufacturer: AMBIENCE FAMILY INC
Category: otc | Type: HUMAN OTC DRUG LABEL
Date: 20240615

ACTIVE INGREDIENTS: BORNEOL 1 mg/8 mL; ZINGIBER MONTANUM ROOT 1 mg/8 mL
INACTIVE INGREDIENTS: MENTHOL; CAMPHOR OIL; SESAME OIL

DOSAGE AND ADMINISTRATION

FOR EXTERNAL USE ONLY.

If swallowed, get medical attention or contact a Poison Center immediately Directions Apply generously of affected areas and massage gently until cream is absorbed in to the skin.

Stop use and ask doctor if Condition worsens.
Servere skin irritation occurs.
Symptoms persist for more than 7 days.
If pregnant or breast-feeding, or if you have sensitive skin, ask a healthcare professional before use.

INACTIVE INGREDIENT

Champor 25%
Menthol 11%

INDICATIONS AND USAGE

Extemal Analgesic

Temporarily relieve body aches and pains of muscles and joints associated with psimple backache parthritis astrains abruises asprains

KEEP OUT OF REACH OF CHILDREN

For adults and children over 12 apply on the affected area not more than 3-4 times daily.
For children under 12 years of age,
consult a doctor before using.

Stop use and ask doctor if Condition worsens.
Servere skin irritation occurs.
Symptoms persist for more than 7 days.

PURPOSE

External Analgesic

ACTIVE INGREDIENT

Zingiber montanum12.5% Extemal Analgesic
Borneol Camphor 12.5%. External Analgesic

PACKAGE LABEL

Yellow Oil
Somthawin (Ang Ki)